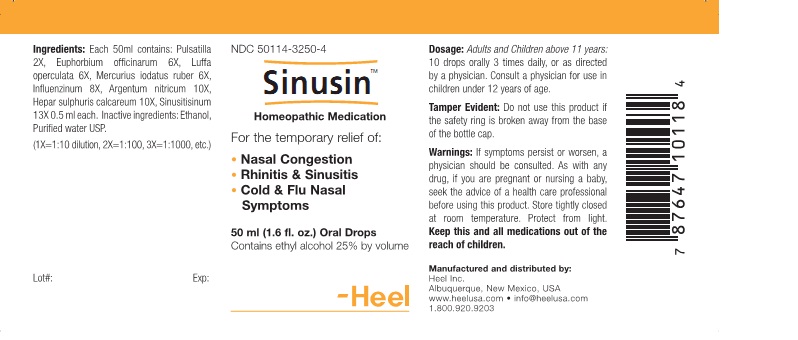 DRUG LABEL: Sinusin
NDC: 50114-3250 | Form: LIQUID
Manufacturer: Heel Inc
Category: homeopathic | Type: HUMAN OTC DRUG LABEL
Date: 20111114

ACTIVE INGREDIENTS: PULSATILLA VULGARIS 2 [hp_X]/50 mL; EUPHORBIA RESINIFERA RESIN 6 [hp_X]/50 mL; LUFFA OPERCULATA FRUIT 6 [hp_X]/50 mL; MERCURIC IODIDE  6 [hp_X]/50 mL; SILVER NITRATE 10 [hp_X]/50 mL; CALCIUM SULFIDE 10 [hp_X]/50 mL; SINUSITISINUM 13 [hp_X]/50 mL; INFLUENZA A VIRUS A/SINGAPORE/6/86 (H1N1) HEMAGGLUTININ ANTIGEN (HEAT INACTIVATED) 8 [hp_X]/50 mL; INFLUENZA A VIRUS A/BEIJING/32/92 (H3N2) HEMAGGLUTININ ANTIGEN (HEAT INACTIVATED) 8 [hp_X]/50 mL; INFLUENZA B VIRUS B/PANAMA/45/90 HEMAGGLUTININ ANTIGEN (HEAT INACTIVATED) 8 [hp_X]/50 mL
INACTIVE INGREDIENTS: ALCOHOL; WATER

SINUSIN Oral Drops

KEEP OUT OF REACH OF CHILDREN

Keep this and all medications out of the reach of children.

INDICATIONS AND USAGE

For the temporary relief of:

- Nasal Congestion
- Rhinitis and Sinusitis
- Cold and Flu Nasal Symptoms

WARNINGS

If symptoms persist or worsen, a physician should be consulted. As with any drug, if you are pregnant or nursing a baby, seek the advise of a health care professional before using this product.

DOSAGE AND ADMINISTRATION

Adults and Children above 11 years: 10 drops orally 3 times daily, or as directed by a physician. Consult a physician for use in children under 12 years of age.

ACTIVE INGREDIENTS

Each 50ml contains: Pulsatilla 2X, Euphorbium officinarum 6X, Luffa operculata 6X, Mercurius iodatus ruber 6X, Influenzinum 8X, Argentum nitricum 10X, Hepar sulphuris calcareum 10X, Sinusitisinum 13X 0.5 ml each.

INACTIVE INGREDIENTS

Ethanol, Purified Water USP

PURPOSE

Nasal Congestion, Rhinitis and Sinusitis, Cold and Flu Nasal Symptoms